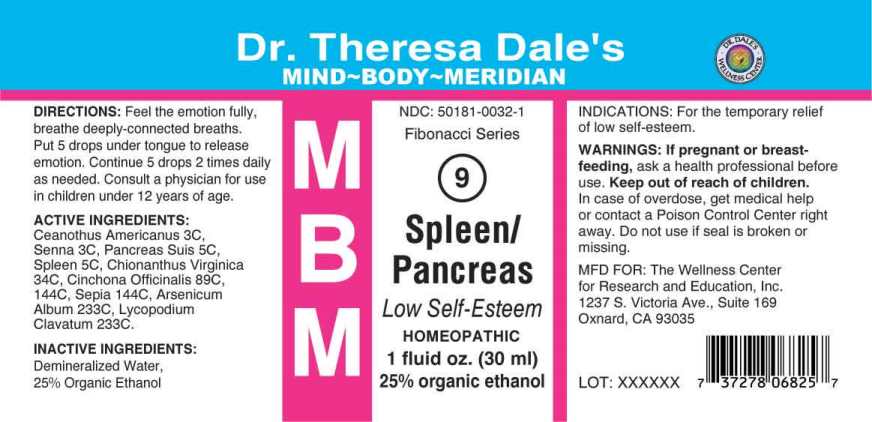 DRUG LABEL: MBM 9 SPLEEN/PANCREAS
NDC: 50181-0032 | Form: LIQUID
Manufacturer: The Wellness Center
Category: homeopathic | Type: HUMAN OTC DRUG LABEL
Date: 20250604

ACTIVE INGREDIENTS: CEANOTHUS AMERICANUS LEAF 3 [hp_C]/1 mL; SENNA LEAF 3 [hp_C]/1 mL; SUS SCROFA PANCREAS 5 [hp_C]/1 mL; SUS SCROFA SPLEEN 5 [hp_C]/1 mL; CHIONANTHUS VIRGINICUS ROOT BARK 34 [hp_C]/1 mL; CINCHONA OFFICINALIS BARK 89 [hp_C]/1 mL; SEPIA OFFICINALIS JUICE 144 [hp_C]/1 mL; ARSENIC TRIOXIDE 233 [hp_C]/1 mL; LYCOPODIUM CLAVATUM SPORE 233 [hp_C]/1 mL
INACTIVE INGREDIENTS: ALCOHOL; WATER

Drug Facts

ACTIVE INGREDIENTS:

Ceanothus Americanus 3C, Senna (Cassia Angustifolia) 3C, Pancreas Suis 5C, Spleen 5C, Chionanthus Virginica 34C, Cinchona Officinalis 89C, 144C, Sepia 144C, Arsenicum Album 233C, Lycopodium Clavatum 233C.

INDICATIONS:

For the temporary relief of low self-esteem.

WARNINGS:

If pregnant or breastfeeding, ask a health professional before use.

Keep out of reach of children. In case of overdose, get medical help or contact a Poison Control Center right away.

Do not use if seal is broken or missing.

Keep out of reach of children. In case of overdose, get medical help or contact a Poison Control Center right away.

DIRECTIONS:

Feel the emotion fully, breathe deeply-connected breaths. Put 5 drops under tongue to release emotion. Continue 5 drops 2 times daily as needed. Consult a physician for use in children under 12 years of age.

INDICATIONS:

For the temporary relief of low self-esteem.

INACTIVE INGREDIENTS:

Demineralized Water, 25% Organic Ethanol

QUESTIONS SECTION:

MFD. FOR: The Wellness Center

for Research and Education, Inc.

1237 S. Victoria Ave., Suite 169

Oxnard, CA 93035

PACKAGE LABEL DISPLAY

Dr. Theresa Dale's

MIND-BODY-MERIDIAN

NDC: 50181-0032-1

Fibonacci Series

MBM

9

Spleen Pancreas

Low Self-Esteem

HOMEOPATHIC

1 fluid oz. (30ml)